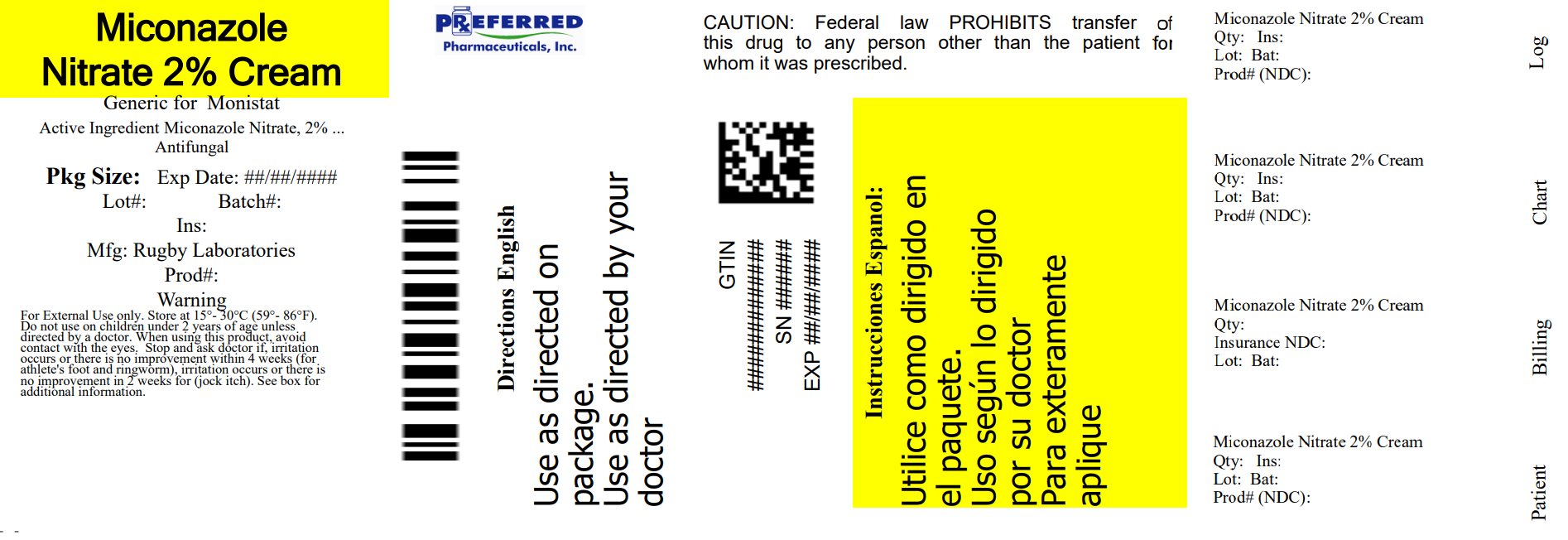 DRUG LABEL: MICONAZOLE Nitrate 2% Cream ANTIFUNGAL
NDC: 68788-8895 | Form: CREAM
Manufacturer: Preferred Pharmaceuticals Inc.
Category: otc | Type: HUMAN OTC DRUG LABEL
Date: 20250801

ACTIVE INGREDIENTS: MICONAZOLE NITRATE 2 g/100 g
INACTIVE INGREDIENTS: CETOSTEARYL ALCOHOL; DIMETHYL SULFOXIDE; EDETATE DISODIUM; ETHYLPARABEN; GLYCERIN; MINERAL OIL; LAURETH-30; WATER; STEARIC ACID; TROLAMINE; PETROLATUM; CARBOMER HOMOPOLYMER, UNSPECIFIED TYPE; GLYCERYL MONO- AND DIPALMITOSTEARATE; ALCOHOL

Rugby Miconazole Nitrate 2%

Active ingredient

Miconazole Nitrate 2%

Purpose

Anti-Fungal

Keep out of reach of children. If swallowed, get medical help or contact a Poison Control Center (1-800-222-1222) immediately.

Uses

- proven clinically effective in the treatment of most athlete's foot (tinea pedis), jock itch (tinea cruris), and ringworm (tinea corporis)
- relieves itching, scaling, cracking, burning and discomfort associated with these conditions.

Warnings

For external use only. Do not use if the safety-sealed tube is punctured or damaged.

Do not use on children under 2 years of age unless directed by a doctor. When using this product avoid contact with the eyes.

Stop use and ask a doctor if • irritation occurs or if there is no improvement within 4 weeks (for athlete's foot and ringworm) • Irritation occurs, or if there is no improvement within 2 weeks (for jock itch).

Other information

Distributed by:
Rugby Laboratories

Indianapolis, IN. 46268

800-616-2471

www.majorpharmaceuticals.com

This product is not manufactured or distributed by Wellspring Pharmaceutical Corporation owner of the registered trademark Micatin.

Directions

Clean the affected area and dry thoroughly • Apply a thin layer of the product over affected area twice daily (morning and night) or as directed by a healthcare professional • Supervise children in the use of this product.

For athlete's foot: • Use daily for 4 weeks. If condition persists, consult a doctor • Pay special attention to the spaces between the toes • Wear well fitting, ventilated shoes • Change socks at least once daily.

For ringworm: Use daily for 4 weeks. If condition persists, consult a doctor.

For jock itch: Use daily for 2 weeks. If condition persists longer, consult a doctor.

This product is not effective on the scalp or nails.

INACTIVE INGREDIENT

Inactive ingredientsCarbomer, alcohol, cetostearyl alcohol, dimethyl sulfoxide, edetate disodium, ethylparaben, glycerol, mineral oil, mono and di glycerides, polyoxyethylene lauryl ether, purified water, stearic acid, triethanolamine, petrolatum.

Other Information

• Store at 15° - 30° c (59° - 86° f) • Lot number and expiration date see crimp of tube or see box. • To open: Unscrew cap, tear safety seal off.

Relabeled By: Preferred Pharmaceuticals Inc.